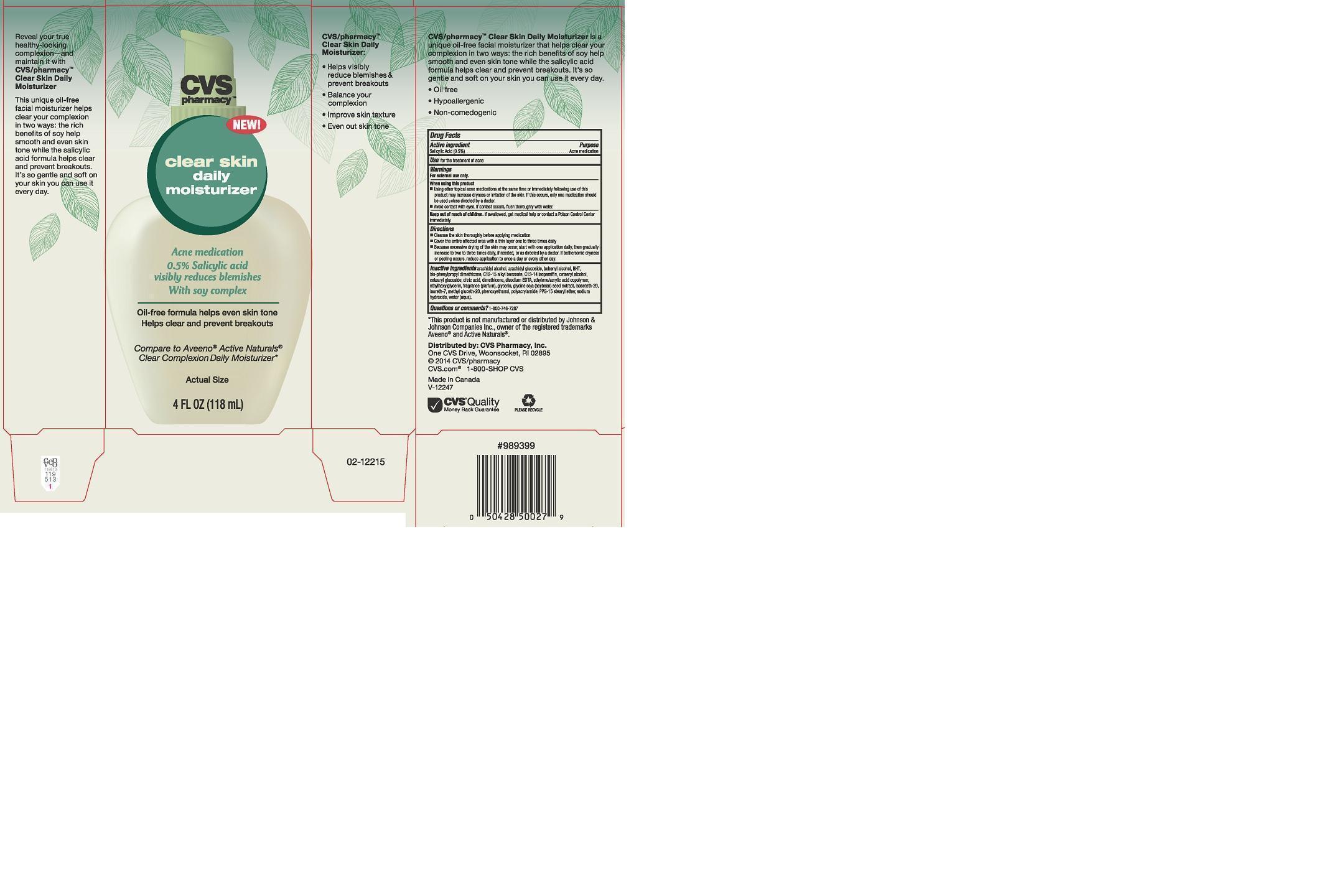 DRUG LABEL: CVS PHARMACY
NDC: 59779-152 | Form: LIQUID
Manufacturer: CVS PHARMACY
Category: otc | Type: HUMAN OTC DRUG LABEL
Date: 20141201

ACTIVE INGREDIENTS: SALICYLIC ACID 5 mg/1 mL
INACTIVE INGREDIENTS: ARACHIDYL ALCOHOL; ARACHIDYL GLUCOSIDE; DOCOSANOL; BUTYLATED HYDROXYTOLUENE; BIS-PHENYLPROPYL DIMETHICONE (15 CST); C12-15 ALKYL BENZOATE; C13-14 ISOPARAFFIN; CETOSTEARYL ALCOHOL; CETEARYL GLUCOSIDE; CITRIC ACID MONOHYDRATE; DIMETHICONE; EDETATE DISODIUM; ETHYLHEXYLGLYCERIN; GLYCERIN; SOYBEAN; ISOCETETH-20; LAURETH-7; METHYL GLUCETH-20; PHENOXYETHANOL; POLYACRYLAMIDE (1300000 MW); PPG-15 STEARYL ETHER; SODIUM HYDROXIDE; WATER

DRUG FACTS

ACTIVE INGREDIENT

SALICYLIC ACID 0.5%

PURPOSE

ACNE MEDICATION

USES

FOR THE TREATMENT OF ACNE

WARNINGS

FOR EXTERNA USE ONLY

WHEN USING THIS PRODUCT

- USING OTHER TOPICAL ACNE MDICATIONS AT THE SAME TIME OR IMMEDIATELY FOLLOWING USE OF THIS PRODUCT MAY INCREASE DRYNESS OR IRRITATION OF THE SKIN. IF THIS OCCURS, ONLY ONE MDICATION SHOULD BE USED UNLESS DIRECTED BY A DOCTOR.
- AVOID CONTACT WITH EYES. IF CONTACT OCCURS, FLUSH THOROUGHLY WITH WATER

KEEP OUT OF REACH OF CHILDREN

IF SWALLOWED, GET MEDICAL HELP OR CONTACT A POISON CONTROL CENTER IMMEDIATELY

DIRECTIONS

- CLEANSE THE SKIN THOROUGHLY BEFORE APPLYING MEDICATION
- COVER THE ENTIRE AFFECTED AREA WITH A THIN LAYER ONE TO THREE TIMES DAILY
- BECAUSE EXCESSIVE DRYING OF THE SKIN MAY OCCUR, START WITH ONE APPLICATION DAILY, THEN GRADUALLY INCREASE TO TWO TO THREE TIMES DAILY, IF NEEDED, OR AS DIRECTED BY A DOCTOR. IF BOTHERSOME DRYNESS OR PEELING OCCURS, REDUCE APLICATION TO ONCE A DAY OR EVERY OTHER DAY

INACTIVE INGREDIENTS

ARACHIDYL ALCOHOL, ARACHIDYL GLUCOSIDE, BEHENYL ALCOHOL, BHT, BIS-PHENYLPROPYL DIMETHICONE, C12-15 ALKYL BENZOATE, C13-14 ISOPARAFFIN, CETEARYL ALCOHOL, CETEARYL GLUCOSIDE, CITRIC ACID, DIMETHICONE, DISODIUM EDTA, ETHYLENE/ACRYLIC ACID COPOLYMER, ETHYLHEXYLGLYCERIN, FRAGRANCE (PARFUM), GLYCERIN, GLYCINE SOJA (SOYBEAN) SEED EXTRACT, ISOCETETH-20, LAURETH-7, METHYL GLUCETH-20, PHENOXYETHANOL, PPG-15 STEARYL ETHER, SODIUM HYDROXIDE, WATER (AQUA)

QUESTIONS OR COMMENTS?

1-800-746-7287